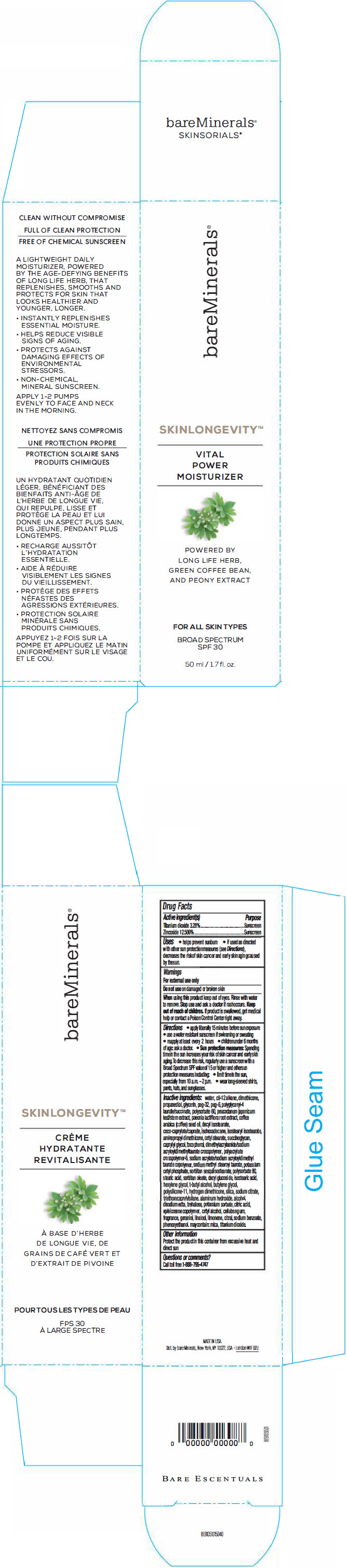 DRUG LABEL: bareMinerals Skinlongevity Vital Power Moisturizer Broad Spectrum SPF 30
NDC: 98132-252 | Form: CREAM
Manufacturer: Orveon Global US LLC
Category: otc | Type: HUMAN OTC DRUG LABEL
Date: 20231004

ACTIVE INGREDIENTS: TITANIUM DIOXIDE 1870 mg/50 mL; ZINC OXIDE 7128 mg/50 mL
INACTIVE INGREDIENTS: CITRIC ACID MONOHYDRATE; VINYLPYRROLIDONE/EICOSENE COPOLYMER; CETYL ALCOHOL; CARBOXYMETHYLCELLULOSE SODIUM, UNSPECIFIED FORM; GERANIOL; LINALOOL, (+/-)-; LIMONENE, (+/-)-; CITRAL; SODIUM BENZOATE; PHENOXYETHANOL; MICA; WATER; DIMETHICONE; PROPANEDIOL; GLYCERIN; POLYETHYLENE GLYCOL 1500; POLYETHYLENE GLYCOL 300; POLYSORBATE 60; ARABICA COFFEE OIL; DECYL ISOSTEARATE; COCO-CAPRYLATE/CAPRATE; ISOHEXADECANE; ISOSTEARYL ISOSTEARATE; CETYL STEARATE; CAPRYLYL GLYCOL; .ALPHA.-TOCOPHEROL; AMMONIUM ACRYLOYLDIMETHYLTAURATE, DIMETHYLACRYLAMIDE, LAURYL METHACRYLATE AND LAURETH-4 METHACRYLATE COPOLYMER, TRIMETHYLOLPROPANE TRIACRYLATE CROSSLINKED (45000 MPA.S); SODIUM ACRYLATE/SODIUM ACRYLOYLDIMETHYLTAURATE COPOLYMER (4000000 MW); SODIUM METHYL STEAROYL TAURATE; SORBITAN SESQUIISOSTEARATE; POTASSIUM CETYL PHOSPHATE; DECYL GLUCOSIDE; POLYSORBATE 80; STEARIC ACID; SORBITAN MONOOLEATE; ISOSTEARIC ACID; HEXYLENE GLYCOL; TERT-BUTYL ALCOHOL; BUTYLENE GLYCOL; HYDROGEN DIMETHICONE (13 CST); SILICON DIOXIDE; SODIUM CITRATE, UNSPECIFIED FORM; TRIETHOXYCAPRYLYLSILANE; ALUMINUM HYDROXIDE; ALCOHOL; EDETATE DISODIUM; TREHALOSE; POTASSIUM SORBATE

bareMinerals® Skinlongevity™ Vital Power Moisturizer Broad Spectrum SPF 30

Drug Facts

ACTIVE INGREDIENT

Active ingredients | Purpose
Titanium Dioxide 3.28% | Sunscreen
Zinc Oxide 12.506% | Sunscreen

Uses

- helps prevent sunburn
- if used as directed with other sun protection measures (see Directions), decreases the risk of skin cancer and early skin aging caused by the sun

Warnings

For external use only

Do not use on damaged or broken skin

When using this product keep out of eyes. Rinse with water to remove.

Stop use and ask a doctor if rash occurs.

Keep out of reach of children. If product is swallowed, get medical help or contact a Poison Control Center right away.

Directions

For sunscreen use:

- apply liberally 15 minutes before sun exposure
- use a water resistant sunscreen if swimming or sweating
- reapply at least every 2 hours
- children under 6 months: ask a doctor
- Sun Protection Measures: Spending time in the sun increases your risk of skin cancer and early skin aging. To decrease this risk, regularly use a sunscreen with a broad spectrum SPF of 15 or higher and other sun protection measures including:
  - limit time in the sun, especially from 10 a.m. – 2 p.m.
  - wear long-sleeve shirts, pants, hats, and sunglasses

Inactive Ingredients

water, c9-12 alkane, dimethicone, propanediol, glycerin, peg-32, peg-6, polyglyceryl-4 laurate/succinate, polysorbate 60, peucedanum japonicum leaf/stem extract, paeonia lactiflora root extract, coffea arabica (coffee) seed oil, decyl isostearate, coco-caprylate/caprate, isohexadecane, isostearyl isostearate, aminopropyl dimethicone, cetyl stearate, succinoglycan, caprylyl glycol, tocopherol, dimethylacrylamide/sodium acryloyldimethyltaurate crosspolymer, polyacrylate crosspolymer-6, sodium acrylate/sodium acryloyldimethyl taurate copolymer, sodium methyl stearoyl taurate, potassium cetyl phosphate, sorbitan sesquiisostearate, polysorbate 80, stearic acid, sorbitan oleate, decyl glucoside, isostearic acid, hexylene glycol, t-butyl alcohol, butylene glycol, polysilicone-11, hydrogen dimethicone, silica, sodium citrate, triethoxycaprylylsilane, aluminum hydroxide, alcohol, disodium edta, trehalose, potassium sorbate, citric acid, vp/eicosene copolymer, cetyl alcohol, cellulose gum, fragrance, geraniol, linalool, limonene, citral, sodium benzoate, phenoxyethanol. may contain: mica, titanium dioxide.

Other information

Protect this product in this container from excessive heat and direct sun.

Questions or comments?

Call toll free 1-800-795-4747

Dist.by bareMinerals, New York, NY 10022, USA

PRINCIPAL DISPLAY PANEL - 50 ml Tube Carton

bareMinerals®

SKINLONGEVITY™

VITAL
POWER
MOISTURIZER

POWERED BY
LONG LIFE HERB,
GREEN COFFEE BEAN,
AND PEONY EXTRACT

FOR ALL SKIN TYPES

BROAD SPECTRUM
SPF30

50 ml / 1.7 fl. oz.